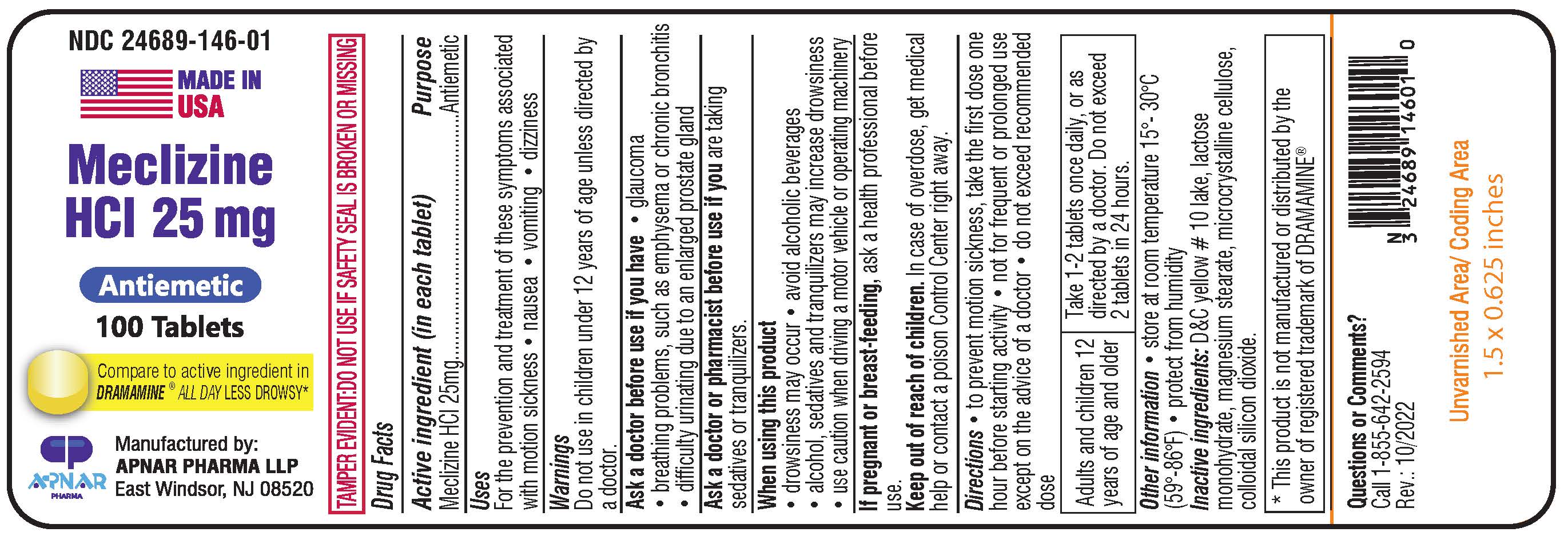 DRUG LABEL: Meclizine Hydrochloride
NDC: 24689-146 | Form: TABLET
Manufacturer: APNAR PHARMA LP
Category: otc | Type: HUMAN OTC DRUG LABEL
Date: 20250109

ACTIVE INGREDIENTS: MECLIZINE HYDROCHLORIDE 25 mg/1 1
INACTIVE INGREDIENTS: SILICON DIOXIDE; LACTOSE MONOHYDRATE; D&C YELLOW NO. 10; CELLULOSE, MICROCRYSTALLINE; MAGNESIUM STEARATE

Meclizine Hydrochloride Tablets 25 mg

Active ingredient (in each tablet)

Meclizine HCL 25 mg

Purpose

Antiemetic

Uses

For the prevention and treatment of these symptoms associated with motion sickness • nausea • vomiting • dizziness

Warnings

Do not use in children under 12 years of age unless directed by a doctor.

Ask a doctor before use if you have

• glaucoma

• breathing problems, such as emphysema or chronic bronchitis

• difficulty urinating due to an enlarged prostate gland

Ask a doctor or pharmacist before use if you are taking sedatives or tranquilizers.

When using this product

• drowsiness may occur

• avoid alcoholic beverages

• alcohol, sedatives and tranquilizers may increase drowsiness

• use caution when driving a motor vehicle or operating machinery

If pregnant or breast-feeding,ask a health professional before use.

Keep out of reach of children. In case of overdose, get medical help or contact a Poison Control Center right away.

Directions

- to prevent motion sickness, take the first dose one hour before starting activity
- not for frequent or prolonged use except on the advice of a doctor
- do not exceed recommended dose

Adults and children 12 years of age and older: Take 1-2 tablets once daily, or as directed by a doctor. Do not exceed 2 tablets in 24 hours.

Other information

- store at room temperature 15˚-30˚C (59˚-86˚F)
- protect from humidity

INACTIVE INGREDIENT

Inactive ingredients: D&C yellow # 10 lake, lactose monohydrate, magnesium stearate, microcrystalline cellulose, colloidal silicon dioxide.

Questions or Comments?

Call 1-855-642-2594

BOXED WARNING

Tamper evident:Do not use if safety seal is broken or missing

Comapre to active ingredient in DRAMAMINE® ALL DAY LESS DROWSY*

*This product is not manufactured or distributed by the owner of registered trademark of DRAMAMINE®

MADE IN USA

Manufactured by:

APNAR PHARMA LLP

East Windsor, NJ 08520

Rev.:10/2022

PACKAGE LABEL

NDC 24689-146-01

Meclizine HCL 25 mg

Antiemetic

100 Tablets